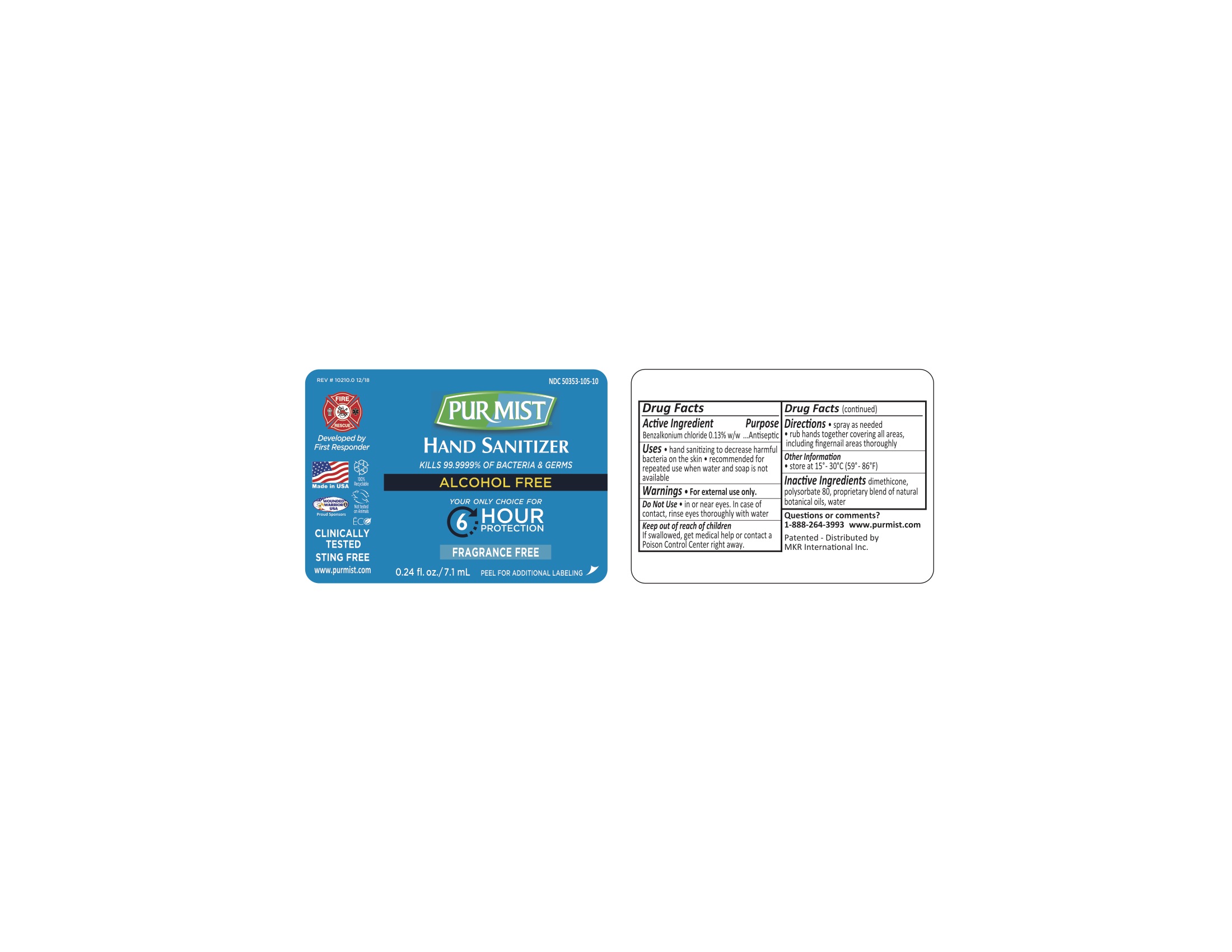 DRUG LABEL: Purmist
NDC: 50353-105 | Form: LIQUID
Manufacturer: MKR International Inc
Category: otc | Type: HUMAN OTC DRUG LABEL
Date: 20210211

ACTIVE INGREDIENTS: BENZALKONIUM CHLORIDE 0.13 g/1 mL
INACTIVE INGREDIENTS: POLYSORBATE 80; WATER; DIMETHICONE

Hand Sanitizer

ACTIVE INGREDIENT

Benzalkonium Cl 0.13%

PURPOSE

Antiseptic

INDICATIONS AND USAGE

Hand sanitizing to decrease harmful bacteria on the skin. Recommended for repeated use when water and soap are not available.

WARNINGS

For external use only. Do not use in or near eyes. In case of contact, rinse eyes thoroughly with water.

KEEP OUT OF REACH OF CHILDREN

If swallowed, get medical help or contact a Poison Control Center right away.

DOSAGE AND ADMINISTRATION

Spray as needed. Rub hands together covering all areas, including fingernail areas thoroughly.

INACTIVE INGREDIENT

Dimethicone, Polysorbate 80, Proprietary blend of natural botanical oils, water.